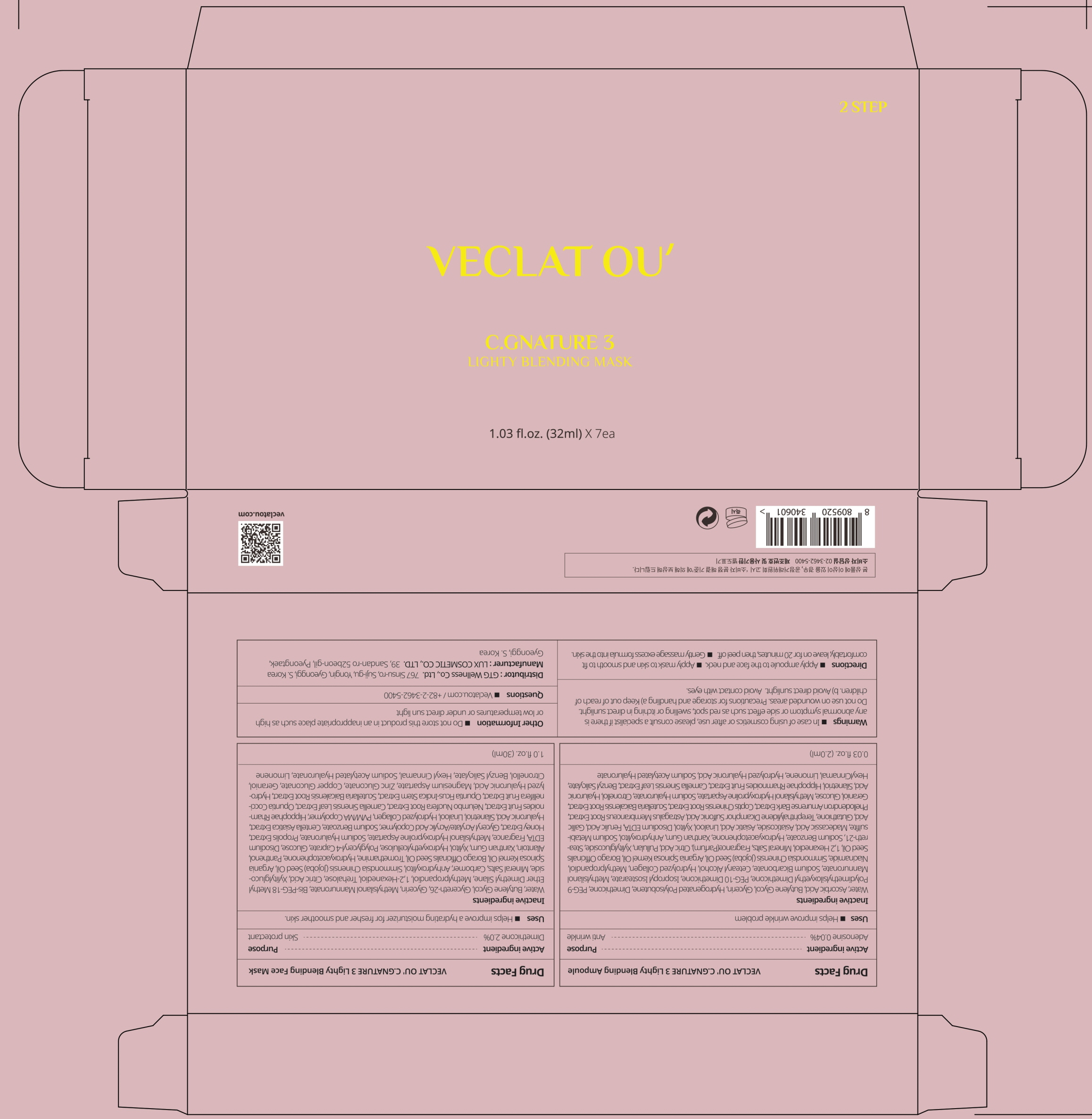 DRUG LABEL: VECLAT OU C.GNATURE 3 Lighty Blending Ampoule
NDC: 71080-0024 | Form: LIQUID
Manufacturer: GTG WELLNESS CO., LTD.
Category: otc | Type: HUMAN OTC DRUG LABEL
Date: 20211124

ACTIVE INGREDIENTS: Adenosine 0.04 g/100 mL
INACTIVE INGREDIENTS: Water; Ascorbic Acid; Butylene Glycol; Glycerin

ACTIVE INGREDIENT

Adenosine 0.04%

INACTIVE INGREDIENTS

Water, Ascorbic Acid, Butylene Glycol, Glycerin, Hydrogenated Polyisobutene, Dimethicone, PEG-9 Polydimethylsiloxyethyl Dimethicone, PEG-10 Dimethicone, Isopropyl Isostearate, Methylsilanol Mannuronate, Sodium Bicarbonate, Cetearyl Alcohol, Hydrolyzed Collagen, Methylpropandiol, Niacinamide, Simmondsia Chinensis (Jojoba) Seed Oil, Argania Spinosa Kernel Oil, Borago Officinalis Seed Oil, 1,2 Hexanediol, Mineral Salts, Fragrance(Parfum), Citric Acid, Pullulan, Xylitylglucoside, Steareth-21, Sodium Benzoate, Hydroxyacetophenone, Xanthan Gum, Anhydroxylitol, Sodium Metabisulfite, Madecassic Acid, Asiaticoside, Asiatic Acid, Linalool, Xylitol, Disodium EDTA, Ferulic Acid, Gallic Acid, Glutathione, Terephthalylidene Dicamphor Sulfonic Acid, Astragalus Membranaceus Root Extract, Phellodendron Amurense Bark Extract, Coptis Chinensis Root Extract, Scutellaria Baicalensis Root Extract, Geraniol, Glucose, Methylsilanol Hydroxyproline Aspartate, Sodium Hyaluronate, Citronellol, Hyaluronic Acid, Silanetriol, Hippophae Rhamnoides Fruit Extract, Camellia Sinensis Leaf Extract, Benzyl Salicylate, Hexyl Cinnamal, Limonene, Hydrolyzed Hyaluronic Acid, Sodium Acetylated Hyaluronate

PURPOSE

Anti wrinkle

WARNINGS

In case of using cosmetics or after use, please consult a specialist if there is any abnormal symptom or side effect such as red spot, swelling or itching in direct sunlight.
Do not use on wounded areas.
Precautions for storage and handling
a) Keep out of reach of children.
b) Avoid direct sunlight.
Avoid contact with eyes.

KEEP OUT OF REACH OF CHILDREN

Uses

■ Helps improve wrinkle problem

Directions

■ Apply ampoule to the face and neck.
■ Apply mask to skin and smooth to fit comfortably, leave on for 20 minutes, then peel off.
■ Gently massage excess formula into the skin.

Other information

■ Do not store this product in an inappropriate place such as high or low temperatures or under direct sun light

Questions

■ Veclatou.com / +82-2-3462-5400